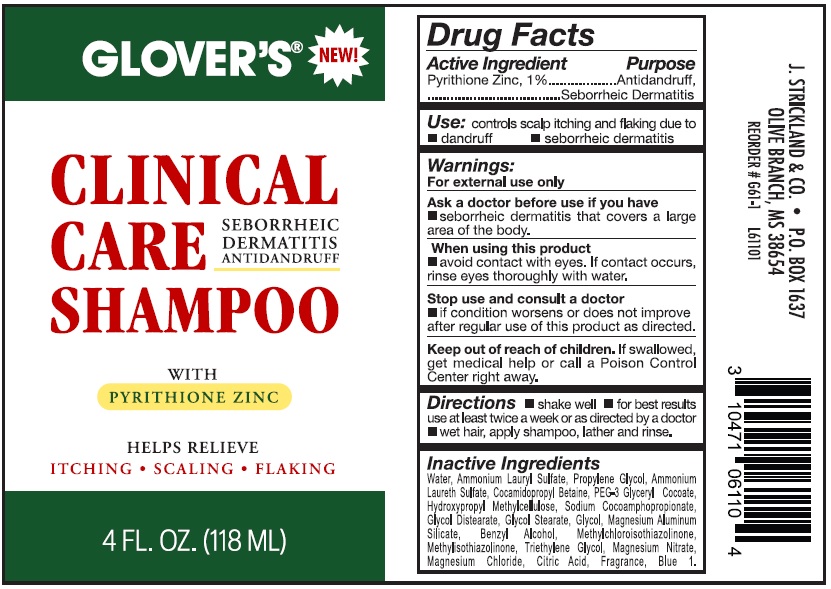 DRUG LABEL: Glovers Clinical Care Seborrheic Dermatitis Antidandruff
NDC: 12022-038 | Form: SHAMPOO
Manufacturer: J. Strickland and Co.
Category: otc | Type: HUMAN OTC DRUG LABEL
Date: 20231021

ACTIVE INGREDIENTS: PYRITHIONE ZINC 10 mg/1 mL
INACTIVE INGREDIENTS: WATER; AMMONIUM LAURYL SULFATE; PROPYLENE GLYCOL; COCAMIDOPROPYL BETAINE; HYPROMELLOSE, UNSPECIFIED; GLYCOL DISTEARATE; GLYCOL STEARATE; ETHYLENE GLYCOL; MAGNESIUM ALUMINUM SILICATE; BENZYL ALCOHOL; METHYLCHLOROISOTHIAZOLINONE; TRIETHYLENE GLYCOL; MAGNESIUM NITRATE; MAGNESIUM CHLORIDE; CITRIC ACID MONOHYDRATE; FD&C BLUE NO. 1; METHYLISOTHIAZOLINONE

Glover's Clinical Care - Seborrheic Dermatitis, Antidandruff - Shampoo

Active Ingredient

Pyrithione Zinc, 1%

Purpose

Antidandruff, Seborrheic Dermatitis

Use:

controls scalp itching and flaking due to

• dandruff • seborrheic dermatitis

Warnings:

For external use only

Ask a doctor before use if you have

• serborrheic dermatitis that covers a large area of the body.

When using this product

• avoid contact with eyes. If contact occurs, rinse eyes thoroughly with water.

Stop use and consult a doctor

if condition worsens or does not improve after regular use of this product as directed.

Keep out of reach of children.

If swallowed, get medical help or call a Poison Control Center right away.

Directions

• shake well • for best results use at least twice a week or as directed by a doctor • wet hair, apply shampoo, lather and rinse.

Inactive Ingredients

Water, Ammonium Lauryl Sulfate, Propylene Glycol, Ammonium Laureth Sulfate, Cocamidopropyl Betaine, PEG-3 Glyceryl Cocoate, Hydroxypropyl Methylcellulose, Sodium Cocoamphopropionate, Glycol Distearate, Glycol Stearate, Glycol, Magnesium Aluminum Silicate, Benzyl Alcohol, Mthylchloriothiazolinone, Triethylene Glycol, Magnesium Nitrate, Magnesium Chloride, Citric Acid, Fragrance, Blue 1.